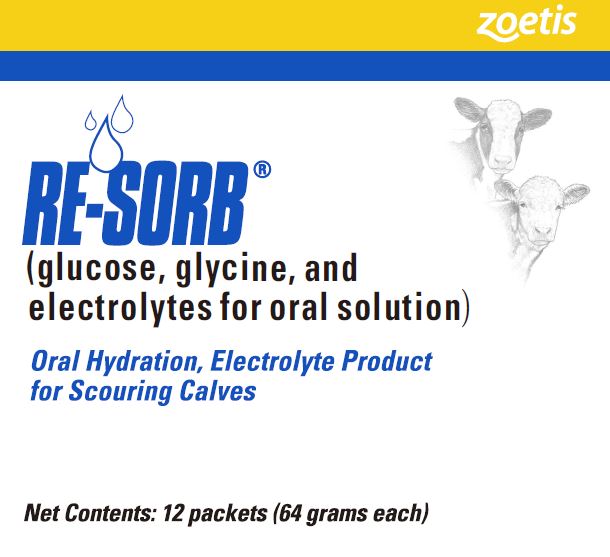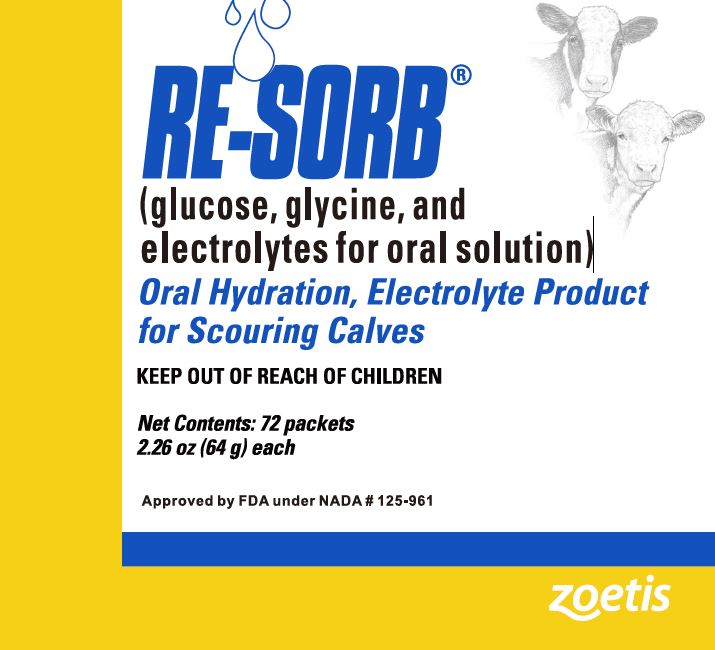 DRUG LABEL: Re-Sorb
NDC: 54771-8112 | Form: POWDER, FOR SOLUTION
Manufacturer: Zoetis Inc.
Category: animal | Type: OTC ANIMAL DRUG LABEL
Date: 20210107

ACTIVE INGREDIENTS: SODIUM CHLORIDE 8.82 g/64 g; POTASSIUM PHOSPHATE, UNSPECIFIED FORM 4.2 g/64 g; SODIUM CITRATE 0.5 g/64 g; POTASSIUM CITRATE 0.12 g/64 g; GLYCINE 6.36 g/64 g; DEXTROSE 44 g/64 g

RE-SORB®

RE-SORB®

(glucose, glycine, and electrolytes for oral solution)
Oral Hydration, Electrolyte Product

DESCRIPTION

The 3 main causes of calf scours and resulting dehydration are bacteria (E. coli and Salmonella, etc.), viruses, and nutritional factors. In all cases, there is a loss of water and electrolytes due to the scours, which can lead to severe dehydration and death. Generally, whatever the cause of the scours, dehydration is the main cause of death. When fecal loss of water exceeds the water intake, dehydration occurs. This can be corrected with administration of either oral or intravenous fluids. In the severely dehydrated calf, intravenous administration is the route of choice.
Oral rehydration is of particular value as it permits the livestock owner to start rehydration therapy at the initial signs of scours which, in many cases, will reduce the severity of the condition. Re-Sorb (glucose, glycine, and electrolytes for oral solution) also provides the owner with a practical method of following up intravenous therapy.
Re-Sorb formula contains the following ingredients: sodium chloride 8.82 grams, potassium phosphate 4.2 grams, citric acid, anhydrous 0.5 grams, potassium citrate 0.12 grams, aminoacetic acid (glycine) 6.36 grams and glucose (dextrose) 44 grams. Osmolarity of the reconstituted solution is approximately 315 m0sm/kg. The pH of the reconstituted solution is approximately 4.3.

Action

Oral glucose/glycine compounds have been used with excellent success to treat dehydration accompanying human cholera for many years.^1–3 The rationale for oral rehydration therapy is based upon the active absorption of glucose and glycine when given orally to scouring animals. Their absorption is linked to the simultaneous absorption of sodium and water. This principle has been verified in scouring animals.^4

E. coli produces scours by secreting toxins in the small intestine. These toxins, while causing profuse secretion of water and electrolytes, have no effect on glucose/glycine absorption in the calf.^5 When Re-Sorb is administered, the glucose/glycine along with the water and sodium are absorbed resulting in a net gain in water thereby correcting the dehydration.

In diarrhea caused by viruses, the disease process causes a flattening of the intestinal mucosa which reduces digestion and absorption of milk. The undigested milk passes into the colon where bacterial fermentation results in additional diarrhea.^6 The replacement of milk with Re-Sorb for 2 days followed by a gradual re-introduction of milk mixed with Re-Sorb, provides an opportunity for the gastrointestinal mucosa to rest.

Since Re-Sorb is readily absorbed, it provides the livestock owner with an ideal first feed for the stressed or newly purchased calf. It is widely believed that it is often beneficial to starve or only provide half of the initial feeding of milk to newly purchased calves to reduce stress on the gastrointestinal system. Re-Sorb may be given as the initial feeding following by a 50:50 mixture of Re-Sorb and milk at the second feeding to reduce stress on the gastrointestinal tract.

INDICATIONS AND USAGE

Re-Sorb (glucose, glycine, and electrolytes for oral solution) is a readily absorbed source of fluids and electrolytes. It is a convenient and effective means of increasing absorption of water, energy sources, and electrolytes. Re-Sorb is indicated for use in the control of dehydration associated with diarrhea (scours) in calves, including veal calves. Re-Sorb may be used by the livestock owner as an early treatment at the first signs of scouring. It may also be used as follow-up treatment for the dehydrated calf following intravenous fluid therapy.
Re-Sorb, because of its ready source of fluid and electrolytes, makes it an ideal first feed (upon arrival) for newly purchased or severely stressed calves.

WARNING

For use in calves only.

Not for Human Use

PRECAUTIONS

Re-Sorb should not be used in animals with severe dehydration (down, comatose, or in a state of shock). Such animals need intravenous fluids since oral therapy in these cases is too slow. A veterinarian should be consulted in such severely scouring calves or in cases requiring antibacterial therapy.

Antibacterial therapy is often indicated in bacterial scours due to E. coli and/or Salmonella. Re-Sorb does not contain antibacterial agents.

Adequate colostrum intake during the first 12 hours is essential for healthy, vigorous calves.

Re-Sorb is not nutritionally complete if administered by itself for long periods of time. It should not be administered beyond the recommended treatment period without the addition of milk or milk replacer.

DOSAGE AND ADMINISTRATION:

Mixing Directions

Add the contents of 1 packet (both sides) to 2 quarts of warm water. Stir until dissolved.

Scouring Calves

Feed 2 quarts of Re-Sorb solution made up as directed, twice daily for 2 days (4 feedings). No milk or milk replacer should be fed during this period. For the next 4 feedings (days 3 and 4), use 1 quart of Re-Sorb solution mixed together with 1 quart of milk or milk replacer. Thereafter, feed as normal.

Newly Purchased Calves

Feed 2 quarts of Re-Sorb solution made up as directed instead of milk as the first feed upon arrival. For the next scheduled feeding, use 1 quart of Re-Sorb solution mixed together with 1 quart of milk or milk replacer. Thereafter, feed as normal.

HOW SUPPLIED

Re-Sorb is supplied in boxes containing 12 packets (double-sided) and in buckets containing 72 packets (double-sided).

STORAGE

Store at controlled room temperature 15°–30°C (59°–86°F).

REFERENCES

1. Nalin DR: GUT 11:768–772, 1970.
2. Pierce NF and Hirshhorn N: WHO Chron 31:87–93, 1977.
3. J Hopkins Med J 132:197–205, 1973.
4. Bywater R: AJVR 38:1983, 1977.
5. Bywater R: J Comp Path 80:565, 1970.
6. Halpin CS and Caple IW: Aust Vet J 52:438, 1976.

Approved by FDA under NADA # 125-961
zoetis

Distributed by:
Zoetis Inc.
Kalamazoo, MI 49007

Revised: November 2020
511291/40032831